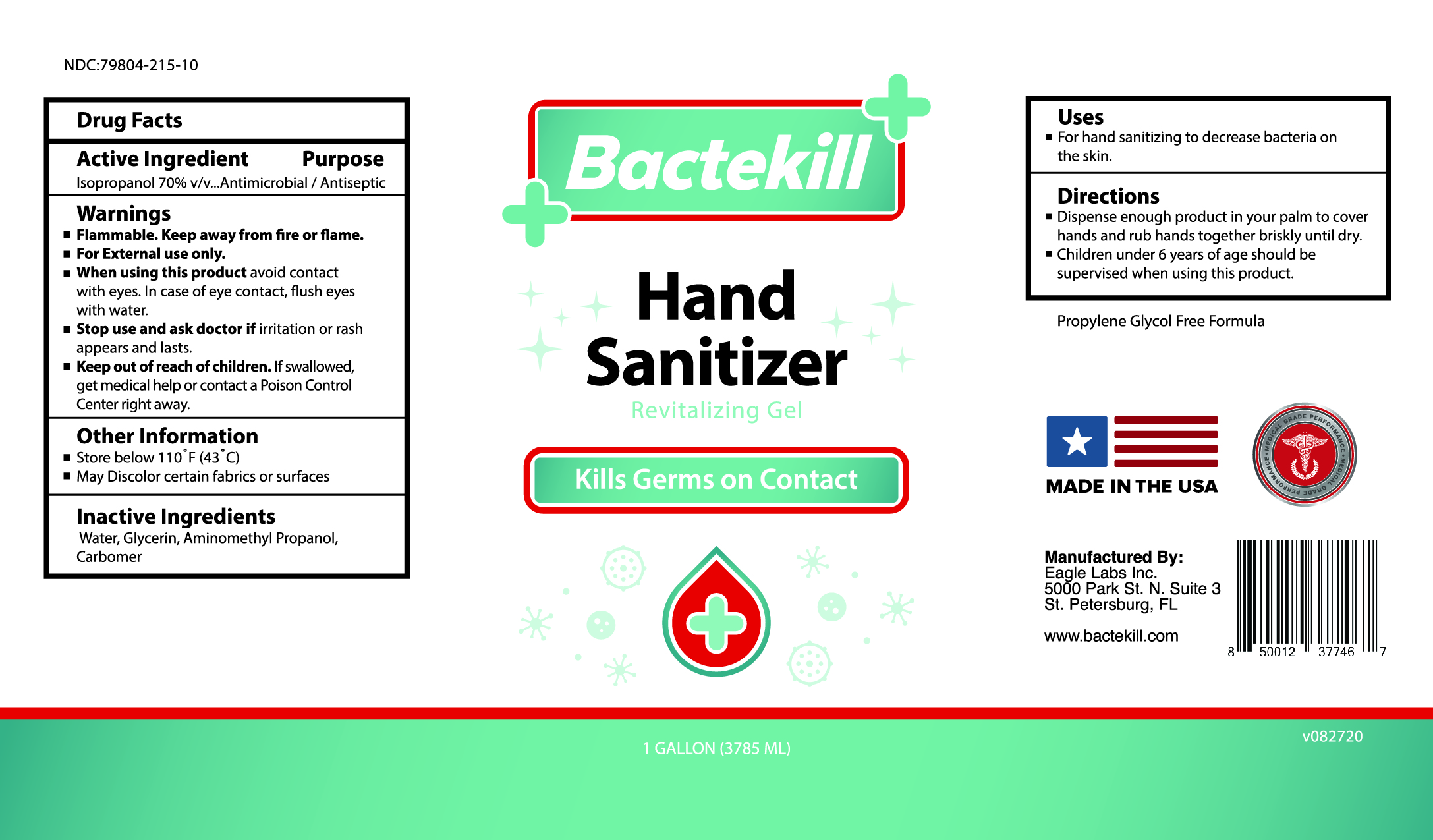 DRUG LABEL: Bactekill Hand Sanitizer
NDC: 79804-215 | Form: GEL
Manufacturer: Eagle Labs
Category: otc | Type: HUMAN OTC DRUG LABEL
Date: 20220210

ACTIVE INGREDIENTS: ISOPROPYL ALCOHOL 0.7 mL/1 mL
INACTIVE INGREDIENTS: Glycerin 1 mL/1 mL; CARBOMER 940 1 mL/1 mL; AMINOMETHYL PROPANEDIOL 1 mL/1 mL

Bactekill Hand Sanitizer 70% IPA Gel

Active Ingredient

Isopropyl Alcohol 70% v/v. Purpose : Antiseptic

Purpose

Hand Sanitizer-Antiseptic

Uses

Hand sanitizing to reduce bacteria on the skin

Warnings

- Flamable. Keep away from fire or flame
- For external use only
- When using this product avoid contact with eyes. In case of eye contact, flush eyes with water
- Stop use and ask a doctor if irritation or rash appears and lasts
- Keep out of reach of children. If swallowed, get medical help or contact a Poison Control Center right away

Do not use

- in children less than 2 months of age
- on open skin wounds

When using

When using this product keep out of eyes, ears and mouth. In case of contact with eyes, rinse, stop use and ask a doctor if irritation or rash occurs. These may be signs of a serious condition. Keep out of reach of children. If swallowed, get medical help or contact a Poison Control Center.

Stop use section

Stop use and ask a doctor if irritation or rash occurs. These may be a sign of a serious condition.

Keep out of reach of children. If swallowed, get medical help or contact a Poison Control Center.

Directions

- Dispense enough product in your palm to cover hands and rub hands together briskly until dry
- Children under 6 years of age should be supervised when using this product

Other information

- Store between 15-30C (59-86F)
- Avoid freesing and excessive heat above 43C (110F)

Inactive ingredients

Glycerin, Carbomer 940, Aminomethyl Propanediol, purified water USP

Package Label- Principal Display Panel

4 FL OZ (118 mL) NDC: 79804-215-04